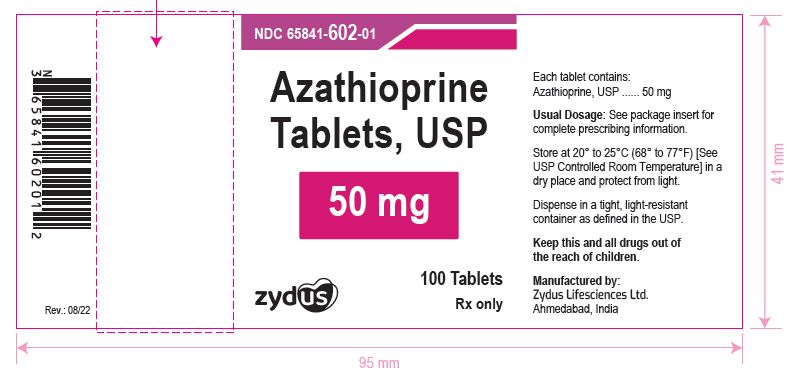 DRUG LABEL: Azathioprine
NDC: 65841-602 | Form: TABLET
Manufacturer: Zydus Lifesciences Limited
Category: prescription | Type: HUMAN PRESCRIPTION DRUG LABEL
Date: 20241125

ACTIVE INGREDIENTS: AZATHIOPRINE 50 mg/1 1
INACTIVE INGREDIENTS: CROSCARMELLOSE SODIUM; LACTOSE MONOHYDRATE; MAGNESIUM STEARATE; POVIDONE; STARCH, CORN

Azathioprine Tablets, USP

PACKAGE LABEL.PRINCIPAL DISPLAY PANEL

NDC 65841-602-01 in bottle of 100 tablets

Azathioprine Tablets USP, 50 mg

100 tablets

Rx only